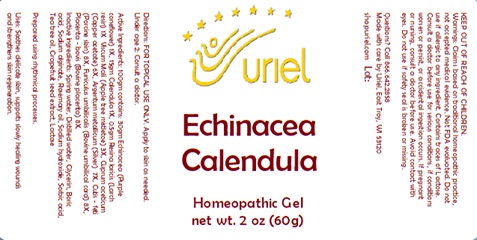 DRUG LABEL: Echinacea Calendula
NDC: 48951-4175 | Form: GEL
Manufacturer: Uriel Pharmacy Inc.
Category: homeopathic | Type: HUMAN OTC DRUG LABEL
Date: 20241122

ACTIVE INGREDIENTS: ECHINACEA, UNSPECIFIED 1 [hp_X]/1 g; CALENDULA OFFICINALIS FLOWERING TOP 1 [hp_X]/1 g; LARIX DECIDUA RESIN 1 [hp_X]/1 g; SUS SCROFA SKIN 8 [hp_X]/1 g; VISCUM ALBUM FRUITING TOP 3 [hp_X]/1 g; SUS SCROFA UMBILICAL CORD 8 [hp_X]/1 g; BOS TAURUS PLACENTA 8 [hp_X]/1 g; CUPRIC ACETATE 6 [hp_X]/1 g; SILVER 7 [hp_X]/1 g
INACTIVE INGREDIENTS: WATER; GLYCERIN; BORIC ACID; CITRUS PARADISI SEED; SODIUM ALGINATE; SORBIC ACID; ROSEMARY OIL; SODIUM HYDROXIDE; TEA TREE OIL

Echinacea Calendula

INDICATIONS AND USAGE

Directions: FOR TOPICAL USE ONLY.

DOSAGE AND ADMINISTRATION

Apply to skin as needed. Under age 2: Consult a doctor.

ACTIVE INGREDIENT

Active Ingredients: 100gm contains: 30gm Echinacea (Purple coneflower) 1X, 15gm Calendula 1X, 0.5gm Resina laricis (Larch resin) 1X; Viscum Mali (Apple tree mistletoe) 3X, Cuprum aceticum (Copper acetate) 6X, Argentum metallicum (Silver) 7X, Cutis - feti (Porcine skin) 8X, Funiculus umbilicalis (Bovine umbilical cord) 8X, Placenta - bovis (Bovine placenta) 8X

INACTIVE INGREDIENT

Inactive Ingredients: Spring water, Distilled water, Glycerin, Boric acid, Sodium alginate, Rosemary oil, Sodium hydroxide, Sorbic acid, Tea tree oil, Grapefruit seed extract, Lactose

Prepared using rhythmical processes.

PURPOSE

Uses: Soothes delicate skin, supports slowly healing wounds and strengthens skin regeneration.

KEEP OUT OF REACH OF CHILDREN.

Warnings: FOR EXTERNAL USE ONLY.
Claims based on traditional homeopathic practice, not accepted medical evidence. Not FDA evaluated. Do not use if allergic to any ingredient. Contains traces of lactose. Consult a doctor before use for serious conditions, if conditions worsen or persist, or accidental ingestion occurs. If pregnant or nursing, consult a doctor before use. Avoid contact with eyes. Do not use if safety seal is broken or missing.

Questions? Call 866.642.2858
Made with care by Uriel, East Troy, WI 53120
shopuriel.com Lot: